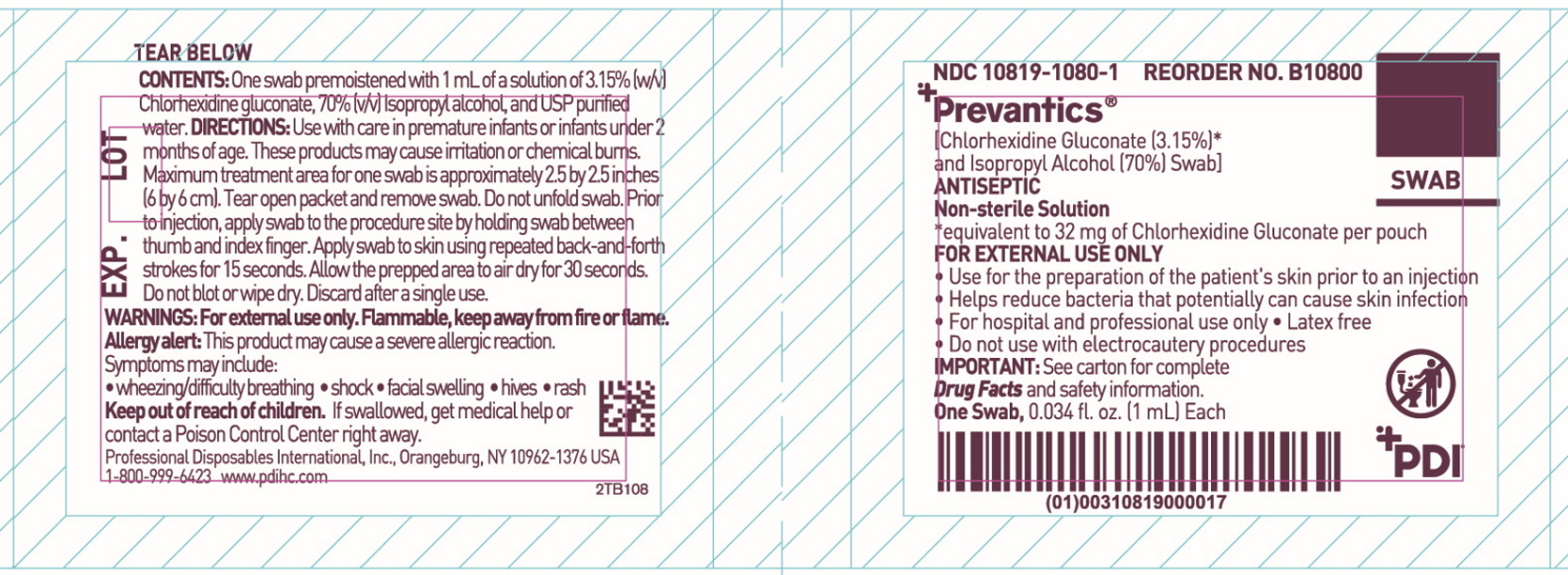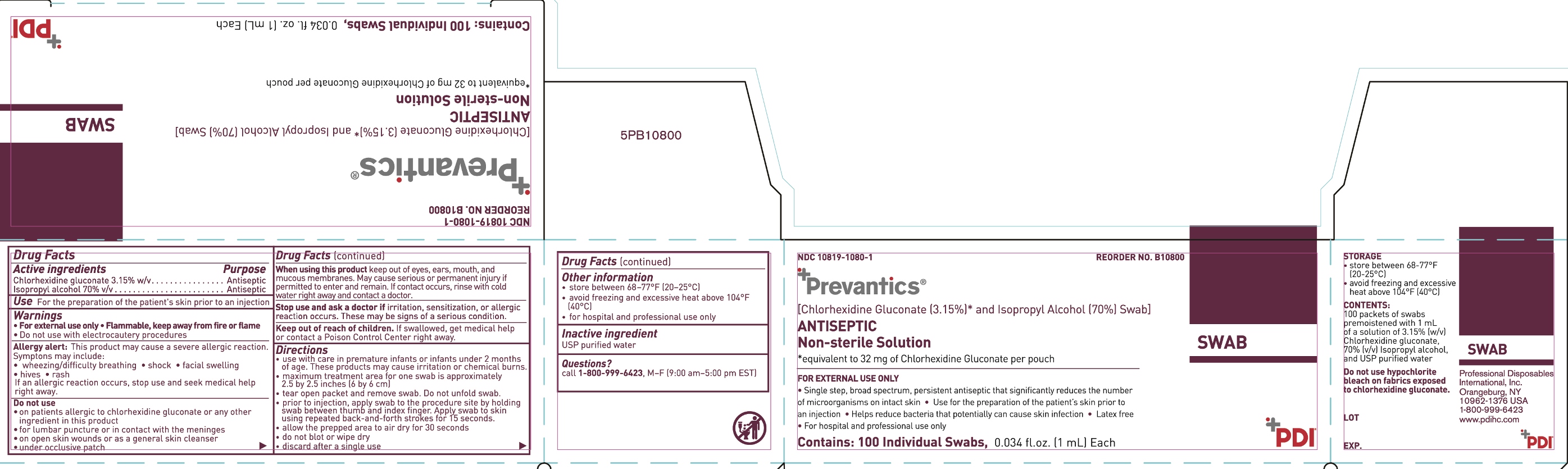 DRUG LABEL: Prevantics Swab
NDC: 10819-1080 | Form: SOLUTION
Manufacturer: Professional Disposables International, Inc.
Category: otc | Type: HUMAN OTC DRUG LABEL
Date: 20231013

ACTIVE INGREDIENTS: CHLORHEXIDINE GLUCONATE 31.5 mg/1 mL; ISOPROPYL ALCOHOL 0.7 mL/1 mL
INACTIVE INGREDIENTS: WATER

B10800 NDC 10819-1080-1

Active ingredients

Chlorhexidine gluconate 3.15% w/v

Isopropyl alcohol 70% v/v

Purpose

Antiseptic

Antiseptic

Use

for the preparation of the patient's skin prior to an injection

Warnings

- For external use only
- Flammable, keep away from fire or flame
- Do not use with electrocautery procedures

Allergy alert

This product may cause a severe allergic reaction. Symptoms may include:

- wheezing/difficulty breathing
- shock
- facial swelling
- hives
- rash

if an allergic reaction occurs, stop use and seek medical help right away

Do not use

- on patients allergic to chlorhexidine gluconate or any other ingredient in this product
- for lumbar puncture or in contact with the meninges
- on open skin wounds or as a general skin cleanser
- under occlusive patch

When using this product

keep out of eyes, ears, mouth and mucous membranes. May cause serious or permanent injury if permitted to enter and remain. If contact occurs, rinse with cold water right away and contact a doctor.

_________________________________________________________________

Stop use and ask a doctor if

irritation, sensitization, or allergic reaction occurs. These may be signs of a serious condition.

Keep out of reach of children.

If swallowed, get medical help or contact a Poison Control Center right away.

Directions

- use with care in premature infants or infants under 2 months of age. These products may cause irritation or chemical burns.
- maximum treatment area for one swab is approximately 2.5 by 2.5 inches (6 by 6 cm)
- tear open packet and remove swab. Do not unfold swab.
- prior to injection, apply swab to the procedure site by holding swab between thumb and index finger. Apply swab to skin using repeated back-and-forth strokes for 15 seconds.
- allow the prepped area to air dry for 30 seconds
- do not blot or wipe dry
- discard after a single use

Other information

- store between 68-77°F (20-25°C)
- avoid freezing and excessive heat above 104°F (40°C)
- for hospital and professional use only

Inactive ingredients

USP purified water

Package/Label Principal Display Panel

Packet Label

Box Label